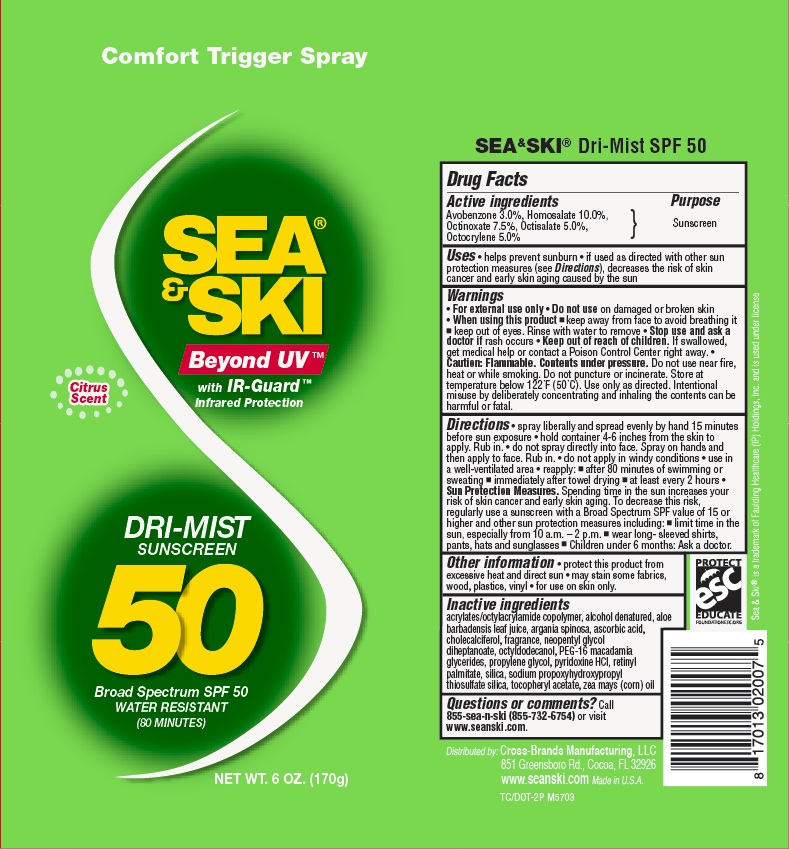 DRUG LABEL: General Protection
NDC: 71153-2007 | Form: AEROSOL, SPRAY
Manufacturer: Cross-Brands Manufacturing LLC
Category: otc | Type: HUMAN OTC DRUG LABEL
Date: 20190108

ACTIVE INGREDIENTS: OCTISALATE 5 g/1 g; HOMOSALATE 10 g/1 g; OCTOCRYLENE 5 g/1 g; OCTINOXATE 7.5 g/1 g; AVOBENZONE 3 g/1 g
INACTIVE INGREDIENTS: ALOE VERA LEAF 0.1 g/1 g

Sea & Ski Cspray 50